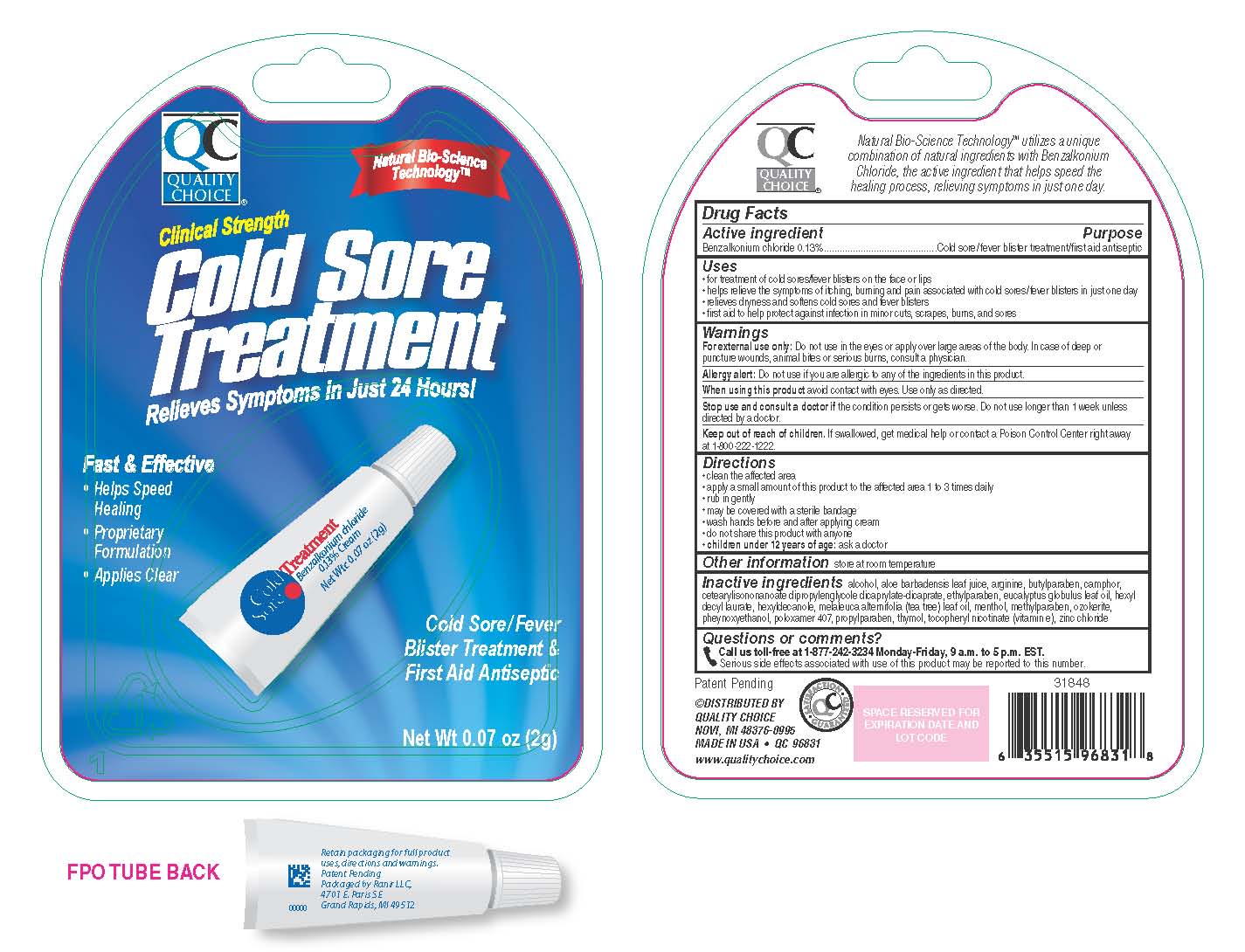 DRUG LABEL: Quality Choice Cold Sore Treatment
NDC: 63868-406 | Form: CREAM
Manufacturer: Chain Drug Marketing Association Inc
Category: otc | Type: HUMAN OTC DRUG LABEL
Date: 20120401

ACTIVE INGREDIENTS: Benzalkonium Chloride 1.3 mg/1 g
INACTIVE INGREDIENTS: Alcohol; Aloe Vera Leaf; Arginine; Butylparaben; Camphor (Synthetic); Cetearyl Isononanoate; Dipropylene Glycol Caprate/Caprylate Diester  ; Ethylparaben; Corymbia Citriodora Leaf Oil; Hexyldecanol; Hexyldecyl Laurate; Levomenthol; Methylparaben; Ceresin; Tea Tree Oil; Poloxamer 407; Propylparaben; Alpha-Tocopherol; Thymol; Zinc Chloride

Drug Facts

Active Ingredient

Benzalkonium Chloride 0.13%

Purpose

Cold Sore/Fever Blister Treatment/First Aid Antiseptic

Uses

- For treatment of cold sores/fever blisters on the face or lips
- Helps relieve the symptoms of itching, burning and pain associated with cold sores/fever blisters in just one day
- Relieves dryness and softens cold sores and fever blisters
- First aid to help protect against infection in minor cuts, scrapes, burns, and sores

Warnings

- For external use only: Do not use in the eyes or apply over large areas of the body. In case of deep or puncture wounds, animal bites or serious burns, consult a physician.
- Allergy Alert: Do not use if you are allergic to any of the ingredients in this product.
- When using this product avoid contact with eyes. Use only as directed.
- Stop use and consult a doctor if the condition persists or gets worse. Do not use longer than 1 week unless directed by a doctor.
- Keep out of reach of children. If swallowed, get medical help or contact a Poison Control Center right away. (1-800-222-1222)

Directions

- Clean the affected area
- Apply a small amount of this product to the affected area 1 to 3 times daily
- Rub in gently
- Wash hands before and after applying cream
- Do not share this product with anyone
- Children under 12 years of age: ask a doctor

Other Information

Store at room temperature

Inactive Ingredients

Alcohol, Aloe Barbadensis Leaf Juice, Arginine, Butylparaben, Camphor, Cetearylisononanoate, Dipropylenglycole Dicaprylate-Dicaprate, Ethylparaben, Eucalyptus Globulus Leaf Oil, Hexyldecanole, Hexyl Decyl Laurate, Menthol,
Methylparaben, Ozokerite, Phenoxyethanol, Melaleuca Alternifolia (Tea Tree) Leaf Oil, Poloxamer 407, Propylparaben, Tocopheryl Nicotinate (Vitamin E), Thymol, Zinc Chloride

Questions or Comments?

Call us toll-free at 1-877-242-3234 Monday-Friday, 9 a.m. to 5 p.m. EST.
Serious side effects associated with use of this product may be reported to this number.

Keep out of reach of children. If swallowed, get medical help or contact a Poison Control Center right away.